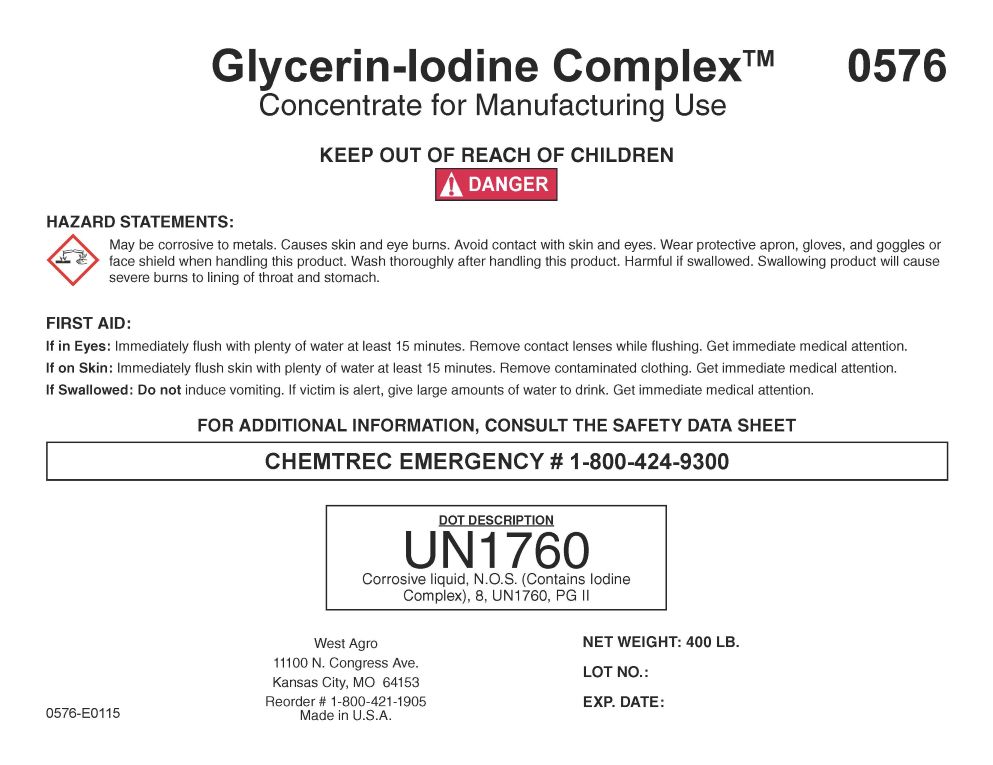 DRUG LABEL: Glycerin-Iodine Complex
NDC: 55756-782 | Form: SOLUTION
Manufacturer: DeLaval, Inc
Category: other | Type: BULK INGREDIENT - ANIMAL DRUG
Date: 20260201

ACTIVE INGREDIENTS: IODINE 1 kg/1 kg
INACTIVE INGREDIENTS: GLYCERIN; WATER; FORMIC ACID; SODIUM HYDROXIDE

Glycerin-Iodine Comples

KEEP OUT OF REACH OF CHILDREN! DANGER

-

HAZARD STATEMENTS:

May be corrosive to metals. Causes skin and eye burns. Avoid contact with skin and eyes. Wear protective apron, gloves and goggles or face shield when handling this product. Wash thoroughly after handling this product. Harmful if swallowed. Swallowed product will cause severe burns to the lining of throat and stomach.

FIRST AID:

If in Eyes: Immediately flush with plenty of water at least 15 minutes. Remove contact lenses while flushing. Get immediate medical attantion.

If on Skin: Immediately flush skin with plenty of water at least 15 minutes. Remove contaminated clothing. Get immediate medical attention.

If Swallowed: Do not induce vomiting. If victim is alert, give large amounts of water to drink. Get immediate medical attention.

FOR ADDITIONAL INFORMATION CONSULT THE SAFETY DATA SHEET

CHEMTREC EMERGENCY # 1-800-424-9300

DOT DECRIPTION

UN1760

Corrosive liquid, N.O.S.

(Contains Iodine Complex), 8, UNI 1760, PG II

HOW SUPPLIED

West Agro, Inc.

11100 N. Congress Ave.

Kansas City, MO 64153

816-891-7700

(M-F, 8:00-4:00 Central time)